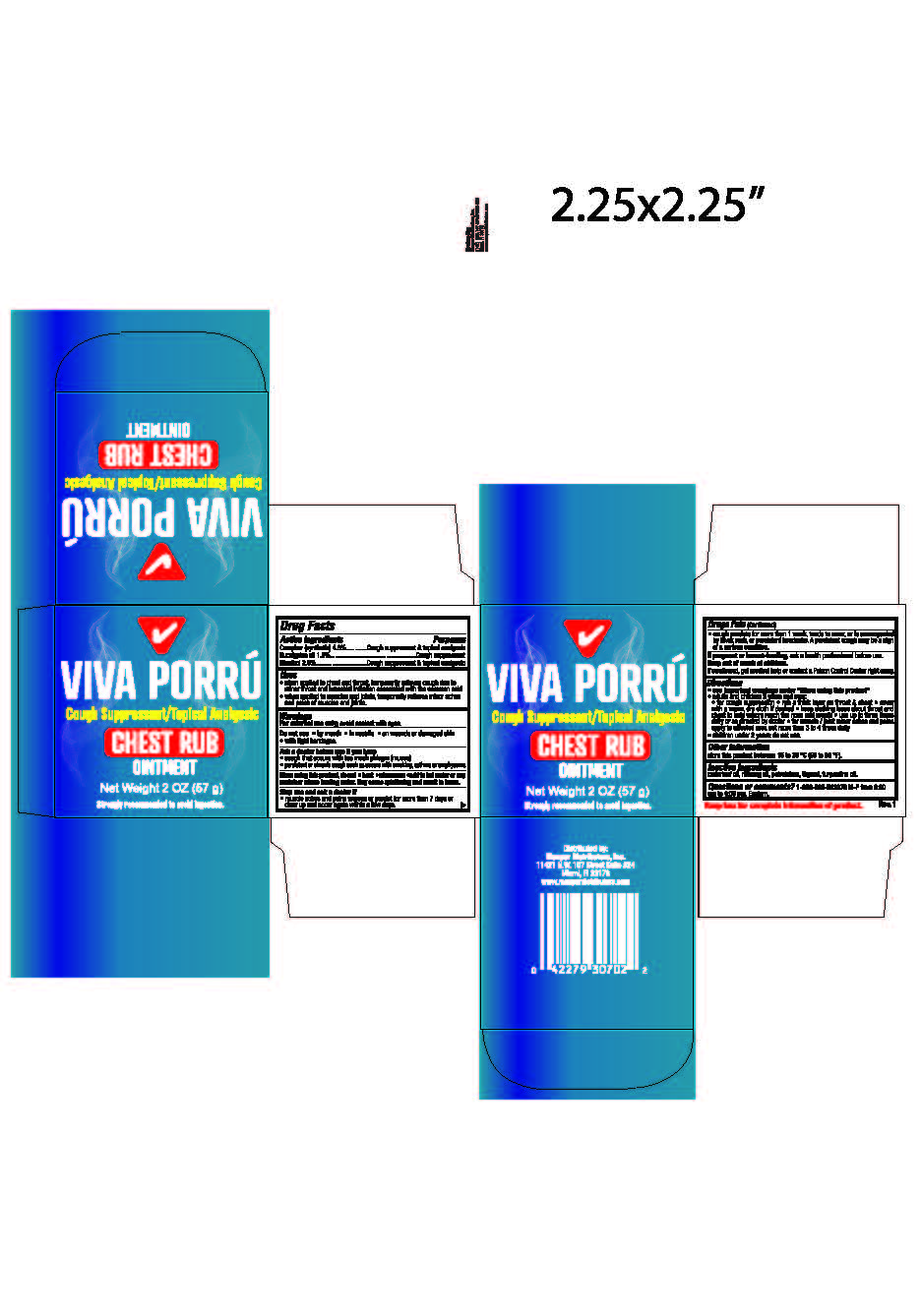 DRUG LABEL: Viva Porru Chest Rub
NDC: 53145-707 | Form: OINTMENT
Manufacturer: Menper Distributors, Inc.
Category: otc | Type: HUMAN OTC DRUG LABEL
Date: 20250722

ACTIVE INGREDIENTS: EUCALYPTUS OIL 0.012 g/1 g; CAMPHOR (SYNTHETIC) 0.048 g/1 g; MENTHOL 0.026 g/1 g
INACTIVE INGREDIENTS: PETROLATUM; CEDAR LEAF OIL; NUTMEG OIL; THYMOL; TURPENTINE OIL

Viva Porrú Chest Rub Ointment

Active Ingredients:

Camphor 4.8 %

Eucalyptus oil 1.2%

Menthol 2.6%

PURPOSE

Cough suppressant & topical analgesic,

Cough suppressant

Cough suppressant & topical analgesic,

Uses

- When applied to chest and throat, temporarily relieves cough due to minor throat and bronchial irritation associated with the common cold.
- When applied to muscles and joints, temporarily relieves minor aches and pains of muscles and joints.

Warnings

For external use only; avoid contact with eyes.

Do not use

- By mouth
- In nostrils
- On wounds or damaged skin
- with tight bandages

Ask A doctor use if you have:

- cough that occurs with too much phlegm (mucus)
- persistent or chronic cough such as occurs with smoking, asthma or emphysema

When using this product, do not

- heat
- Microware
- add to hot water or any container where heating water may cause splattering and result in burns

Stop use and ask a doctor if:

- muscle aches and pains worsen or persist for more than 7 days or clear up and occur again within a few days
- cough persists for more than 1 week, tends to recur, or is accompanied by fever rash, or persistent headache. A persistent cough may be a sign of a serious condition.

If pregnant or breastfeeding

ask a health professional before use

Keep Out Of reach of children

If swallowed, get medical help or contact Poison Control Center right away.

Directions:

See important warnings above

- Adults and children 2 years and over:
- for cough suppression -rub a thick layer on throat and chest - cover with a warm dry cloth if desired- keep clothing loose about throat and chest to help vapors reach the nose and mouth - use up to three times daily or as directed by doctor
- for muscle/joint minor aches and pains apply to affected area not more than 3 to 4 times daily
- children under 2 years: do not use

Other Information

Store at room temperature 15 to 30 o C (59 to 86o F)

Inactive ingredients:

Cedar leaf oil, nutmeg oil, petrolatum, thymol, turpentine oil.